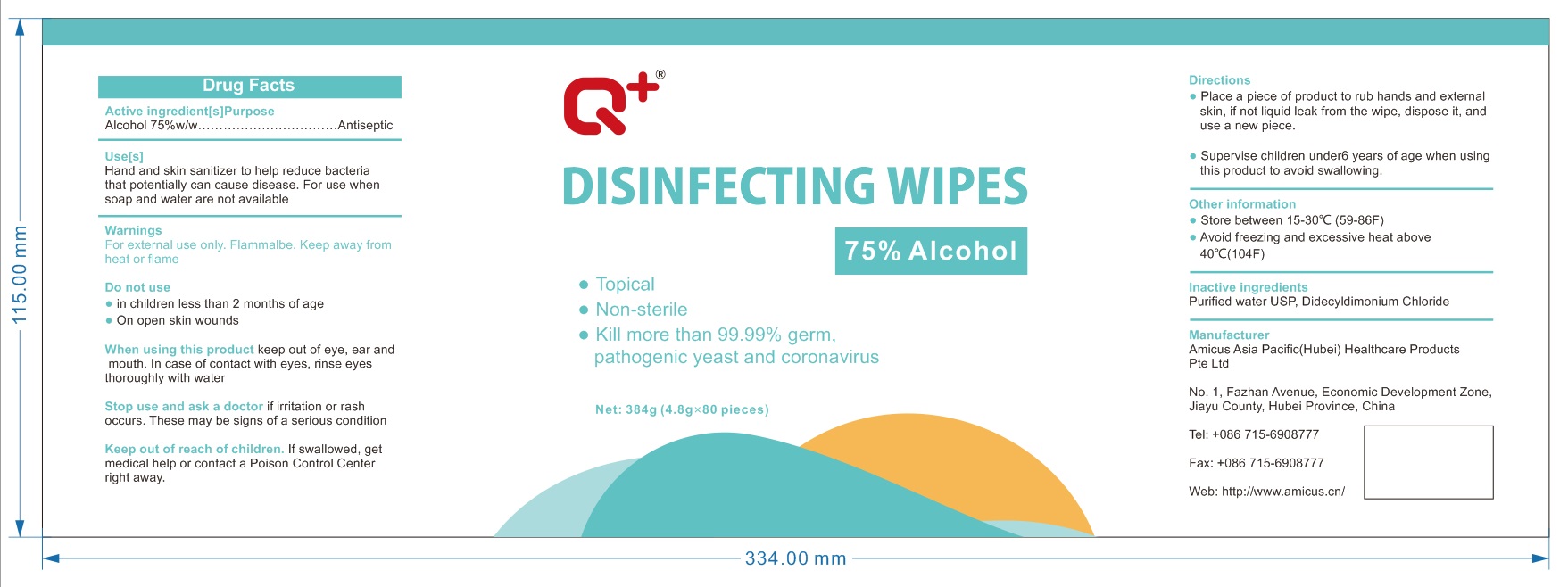 DRUG LABEL: DISINFECTING WIPES
NDC: 54345-003 | Form: CLOTH
Manufacturer: Amicus Asia Pacific(Hubei) Healthcare Products Pte Ltd
Category: otc | Type: HUMAN OTC DRUG LABEL
Date: 20200703

ACTIVE INGREDIENTS: ALCOHOL 60 g/80 1
INACTIVE INGREDIENTS: DIDECYLDIMONIUM CHLORIDE; WATER

DOSAGE AND ADMINISTRATION

●Store between 15-30°C (59-86°F)
●Avoid freezing and excessive heat above 40°C(104°F)

INACTIVE INGREDIENT

Purified water USP, Didecyldimonium Chloride

INDICATIONS AND USAGE

Place a piece of product to rub hands and external skin, if not liquid leak from the wipe, dispose it, and use a new piece.

ACTIVE INGREDIENT

Alcohol

keep out of reach of children

PURPOSE

Disinfection
Sterilization
No Rinseing

WARNINGS

For extermal use only. Flammalbe. Keep away from heat or flame